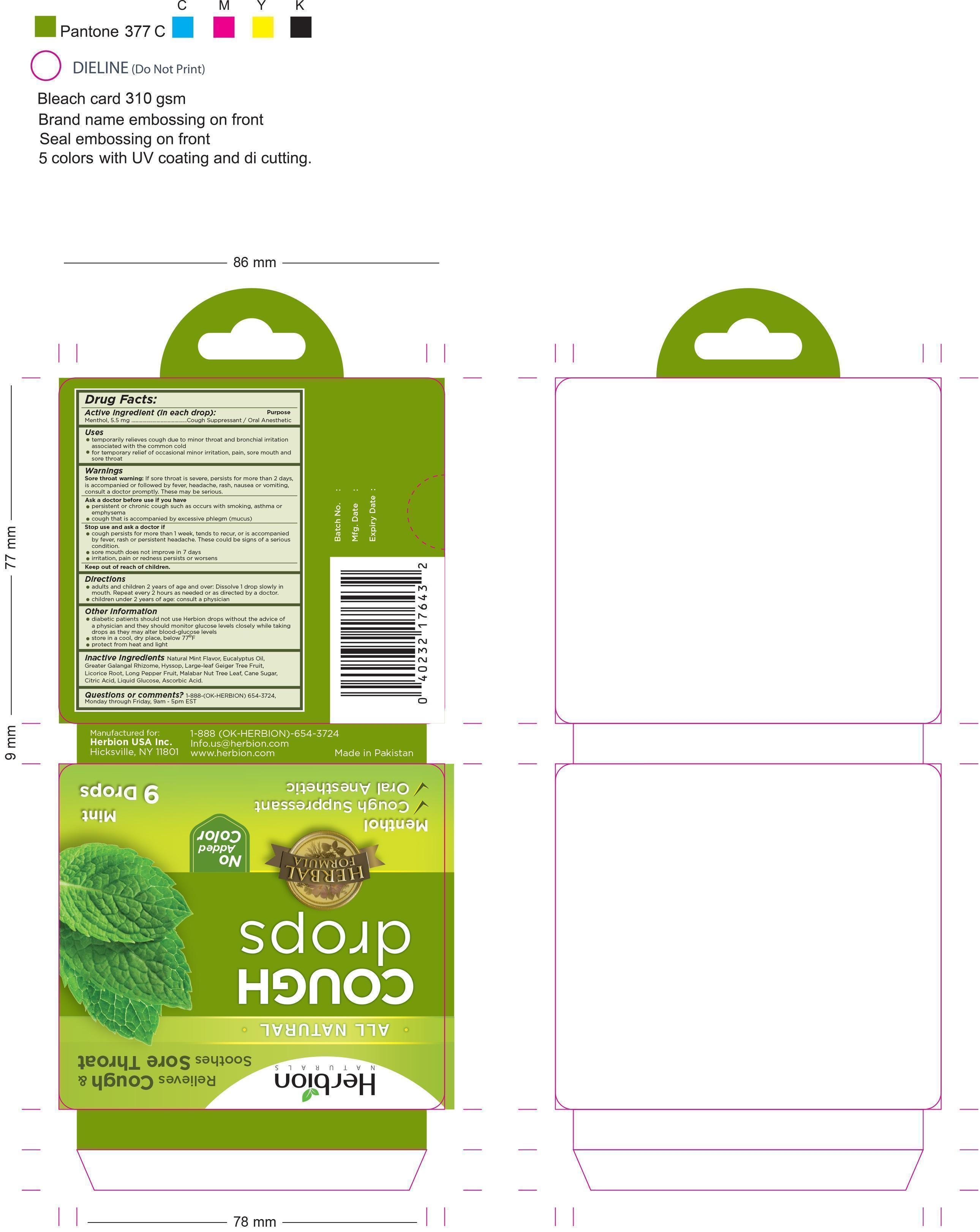 DRUG LABEL: Herbion Naturals Mint  Cough drops
NDC: 44237-022 | Form: LOZENGE
Manufacturer: Herbion Pakistan (pvt) Ltd
Category: otc | Type: HUMAN OTC DRUG LABEL
Date: 20181226

ACTIVE INGREDIENTS: MENTHOL 5.5 mg/2.5 1
INACTIVE INGREDIENTS: ASCORBIC ACID; SUGARCANE; CITRIC ACID MONOHYDRATE; EUCALYPTUS OIL; GREATER GALANGAL; HYSSOPUS OFFICINALIS WHOLE; CORDIA SEBESTENA FLOWER; GLYCYRRHIZA GLABRA; DEXTROSE; LONG PEPPER; JUSTICIA ADHATODA LEAF

Active ingredient (in each drop):

Menthol, 5.5mg

Purpose:

Cough suppressant / Oral Anesthetic

Uses:

- temporarily relieves cough due to minor throat and bronchial irritation associated with the common cold
- for temporary relief of occasional minor irritation, pain, sore mouth and sore throat

WARNINGS

Sore throat warning:

If sore throat is severe, persists for more than 2 days, is accompanied or followed by fever, headache, rash, nausea or vomiting, consult a doctor promptly.These may be serious

Ask a doctor before use if you have:

- persistent or chronic cough such as occurs with smoking, asthma or emphysema
- cough that is accompanied by excessive phlegm (mucus)

Stop use and ask a doctor if:

- cough persists for more than 1 week, tends to recur, or is accompanied by fever, rash, or persistent headache. These could be signs of a serious condition
- sore mouth does not improve in 7 days
- irritation, pain or redness persists or worsens

keep out of reach of children

Directions:

- adults and children 2 years of age and over Dissolve 1 drop slowly in mouth. Repeat every 2 hours as needed or as directed by a doctor
- children under 2 years of age: consult a physician

Other Information:

- diabetic patients should not use Herbion drops without the advice of a physician and they should monitor glucose levels closely while taking drops as they may alter blood-glucose levels
- store in a cool, dry place, below 77°F
- protect from heat and light

Inactive Ingredients:

Natural mint flavor, Eucalyptus oil, Greater galangal Rhizome, Hyssop, Large-leaf geiger tree Fruit, Licorice Root, Long pepper Fruit, Malabar nut tree Leaf,Cane sugar, Citric acid , Liquid glucose, Ascorbic Acid

Questions or Comments?

1-888-(OK-HERBION) 654-3724, Monday through Friday 9am - 5am EST